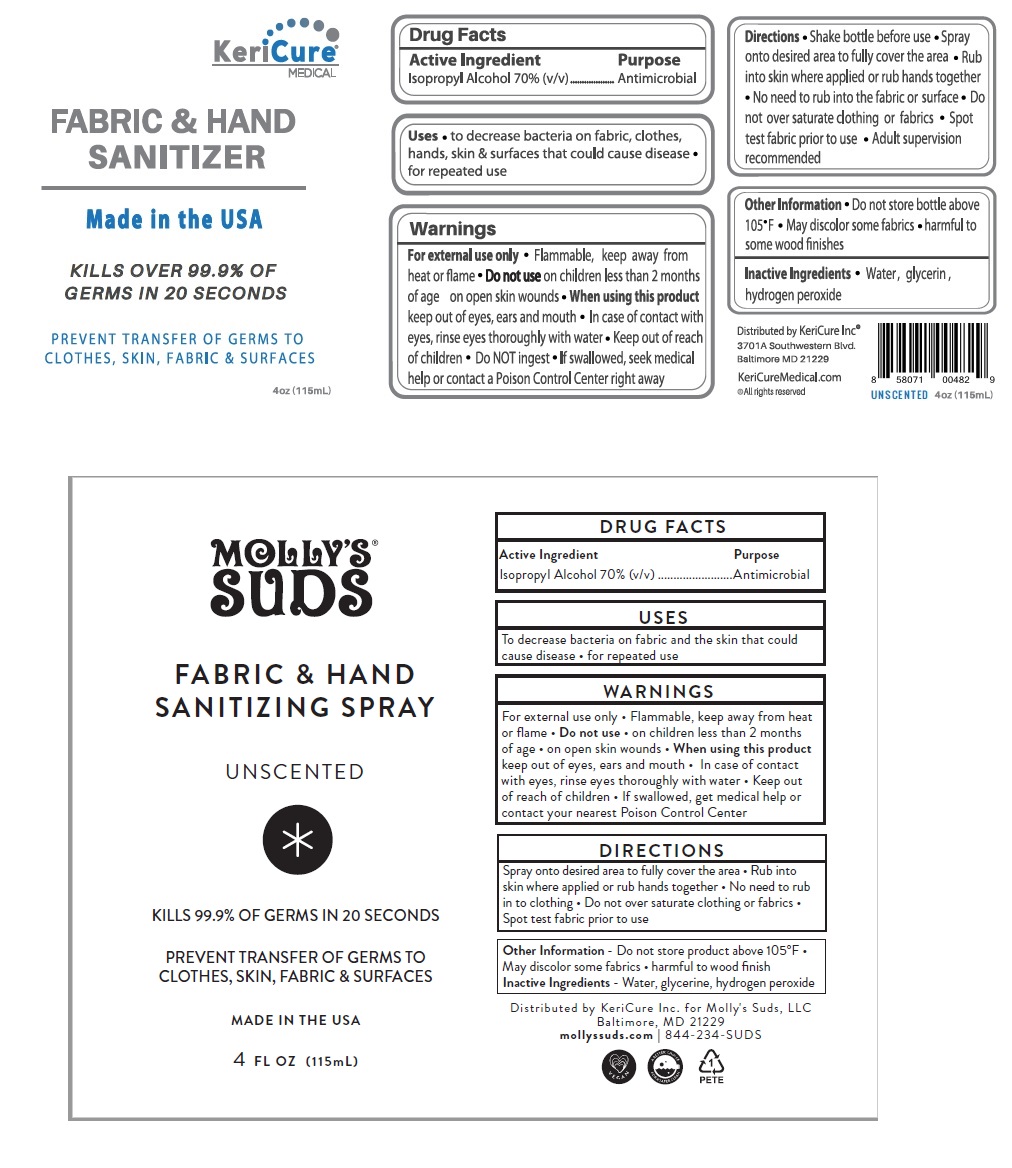 DRUG LABEL: KeriCure Fabric and Hand Sanitizer
NDC: 78280-306 | Form: SPRAY
Manufacturer: Kericure Inc.
Category: otc | Type: HUMAN OTC DRUG LABEL
Date: 20200703

ACTIVE INGREDIENTS: ISOPROPYL ALCOHOL 70 mL/100 mL
INACTIVE INGREDIENTS: WATER; GLYCERIN; HYDROGEN PEROXIDE

KeriCure MEDICAL FABRIC AND HAND SANITIZER

Active Ingredient

Isopropyl Alcohol 70% (v/v)

Purpose

Antimicrobial

INDICATIONS AND USAGE

Uses • to decrease bacteria on fabrics, clothes, hands, skin & surfaces that could cause disease • for repeated use

Warnings

For external use only • Flammable, Keep away from heat or flame • Do not use on children less than 2 months of age on open skin wounds • When using this product keep out of eyes, ears and mouth • In case of contact with eyes, rinse eyes thoroughly with water • do NOT ingest • If swallowed, seek medical help or contact a Poison Control Center right away

• Keep out of reach of children

DOSAGE AND ADMINISTRATION

Directions • Shake bottle before use • Spray onto desired area to fully cover the area • Rub into skin where applied or rub hands together • No need to rub into the fabric or surface • Do not over saturate clothing or fabrics • Spot test fabrics prior to use • Adult supervision recommended

Other Information • Do not store bottle above 105°F • May discolor some fabrics • harmful to some wood finishes

Inactive Ingredients • Water, glycerin, hydrogen peroxide

Made in the USA

KILLS MORE THAN 99.9% OF GERMS

UNSCENTED

PREVENT TRANSFER OF GERMS TO CLOTHES, FABRICS, HANDS & SURFACES

KeriCureMedical.com

® KeriCure Inc • All rights reserved

Distributed by KeriCure Inc

3701A Southwestern Blvd. Baltimore MD 21229